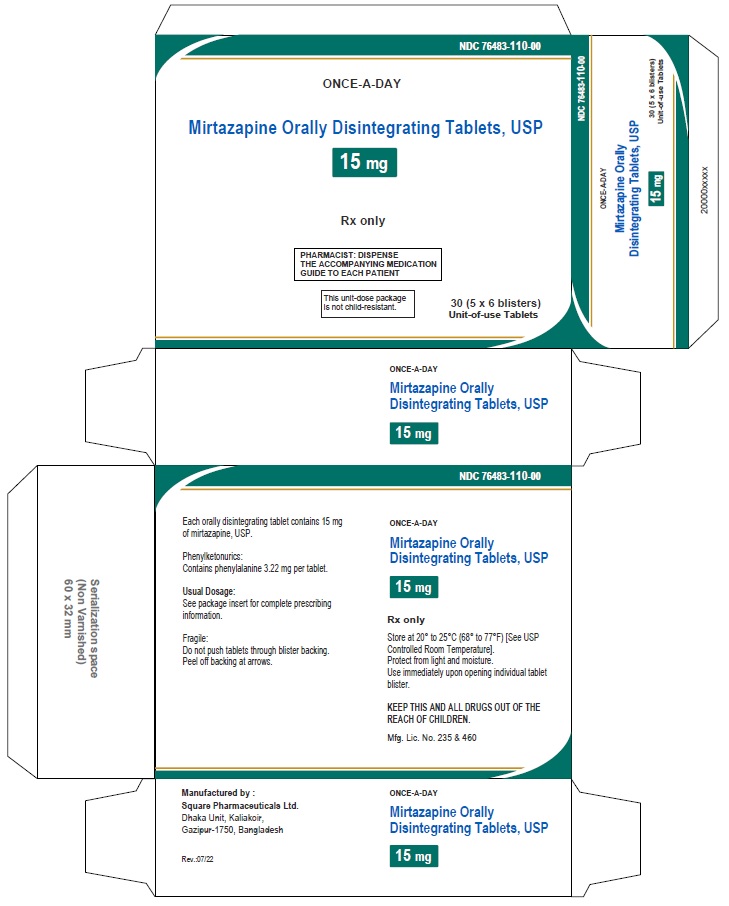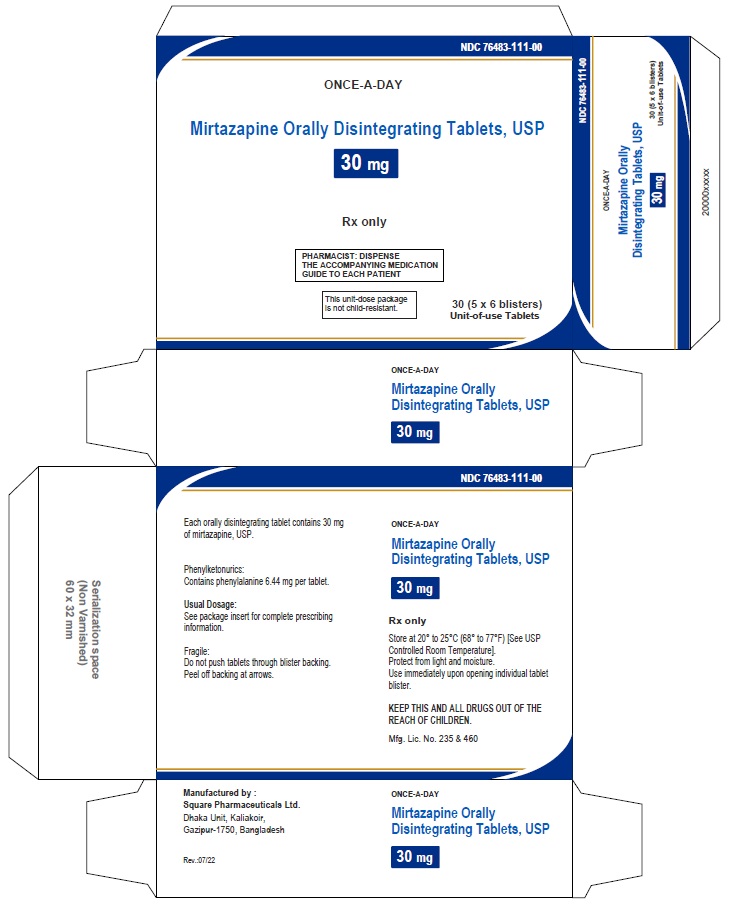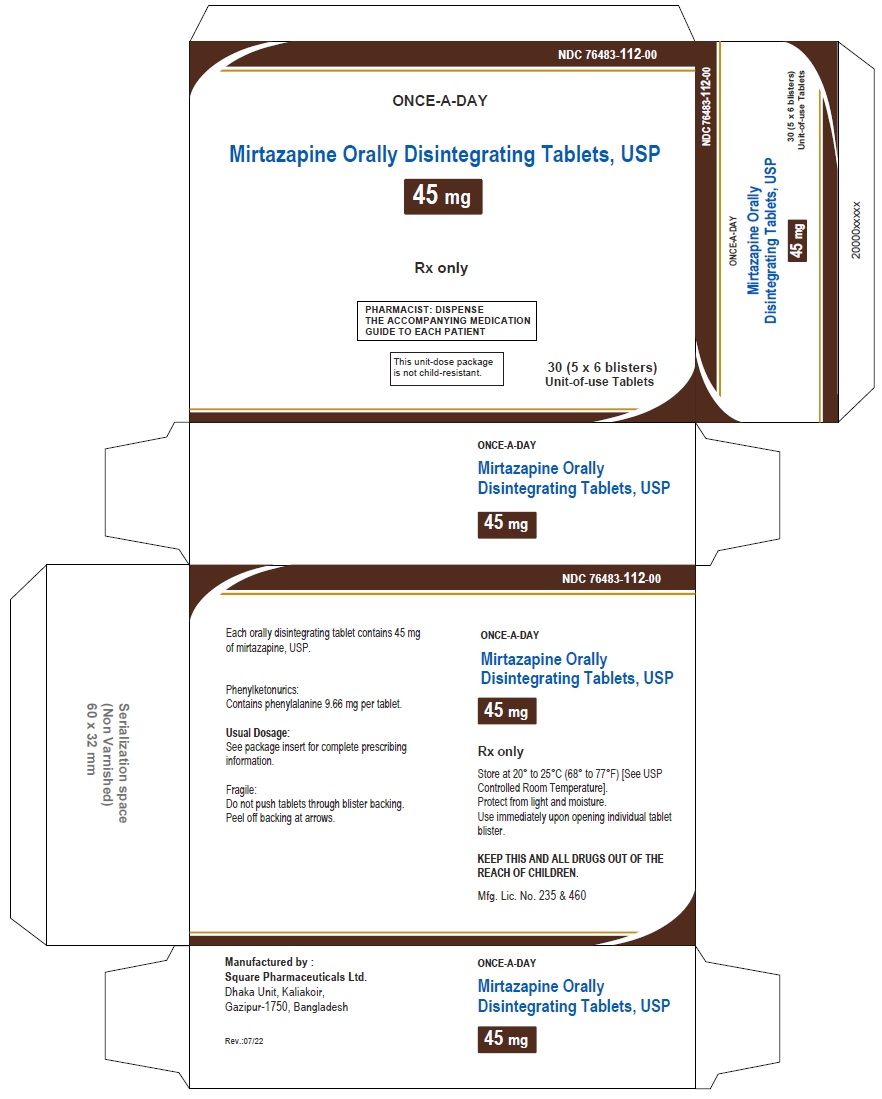 DRUG LABEL: Mirtazapine
NDC: 76483-110 | Form: TABLET, ORALLY DISINTEGRATING
Manufacturer: SQUARE PHARMACEUTICALS LIMITED
Category: prescription | Type: HUMAN PRESCRIPTION DRUG LABEL
Date: 20230702

ACTIVE INGREDIENTS: MIRTAZAPINE 15 mg/1 1
INACTIVE INGREDIENTS: MANNITOL; MICROCRYSTALLINE CELLULOSE; CROSPOVIDONE; POVIDONE K30; ASPARTAME; ALPHA-TOCOPHEROL; MALTODEXTRIN; SILICON DIOXIDE; ANHYDROUS CITRIC ACID; MAGNESIUM STEARATE; SODIUM STEARYL FUMARATE

MIRTAZAPINE ORALLY DISINTEGRATING TABLETS

PACKAGE LABEL.PRINCIPAL DISPLAY PANEL

NDC 76483-110-00 in unit-dose blister cartons of 30 (5 x 6 blisters) Unit-of-use Tablets

Mirtazapine Orally Disintegrating Tablets USP, 15 mg

Rx only

30 Tablets

NDC 76483-111-00 in unit-dose blister cartons of 30 (5 x 6 blisters) Unit-of-use Tablets

Mirtazapine Orally Disintegrating Tablets USP, 30 mg

Rx only

30 Tablets

NDC 76483-112-00 in unit-dose blister cartons of 30 (5 x 6 blisters) Unit-of-use Tablets

Mirtazapine Orally Disintegrating Tablets USP, 45 mg

Rx only

30 Tablets